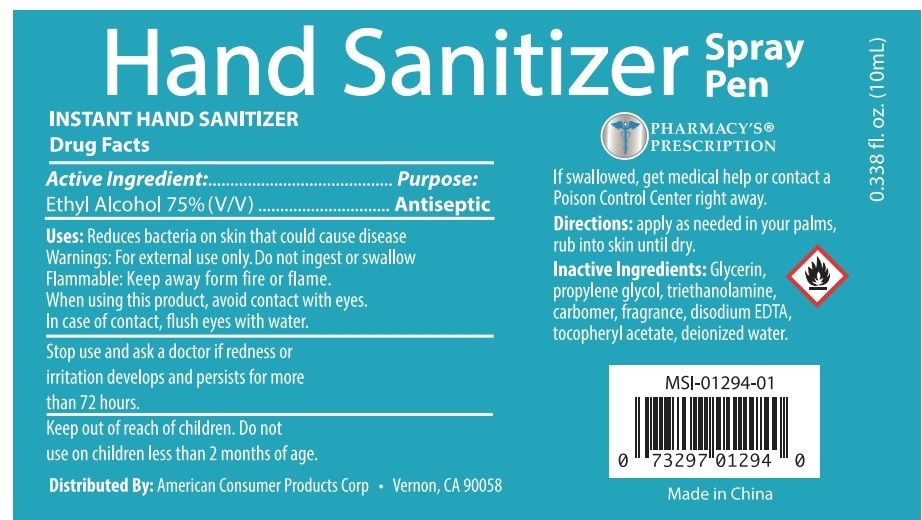 DRUG LABEL: HAND SANITIZER PEN
NDC: 75613-012 | Form: SPRAY
Manufacturer: Ningbo Lanzi Cosmetic Technology Co., Ltd
Category: otc | Type: HUMAN OTC DRUG LABEL
Date: 20201209

ACTIVE INGREDIENTS: ALCOHOL 75 mL/100 mL
INACTIVE INGREDIENTS: WATER; PROPYLENE GLYCOL; EDETATE DISODIUM; TROLAMINE; .ALPHA.-TOCOPHEROL ACETATE, D-; GLYCERIN

HAND SANITIZER

Active ingredient

Ethyl Alcohol 75% (V/V)

Purpose

Antiseptic

Use

Reduces bacteria on skin that could cause disease

Warnings

For external use only

Do not ingest or swallow

Flammable. Keep away from fire and flame.

When using this product

avoid contact with eyes. In case of contact, flush eyes with water.

Stop use and ask a doctor if redness or irritation develops and persists for more than 72 hours.

Do not use on children less than 2 months of age.

Keep out of reach of children.

If swallowed, get medical help or contact a Poison Control Center right away.

Directions

Apply as needed in your palms, rub into skin until dry.

Inactive ingredients

Glycerin, Propylene Glycol, Triethanolamine, Carbomer, Fragrance, Disodium EDTA, tocopheryl acetate, Deionized Water